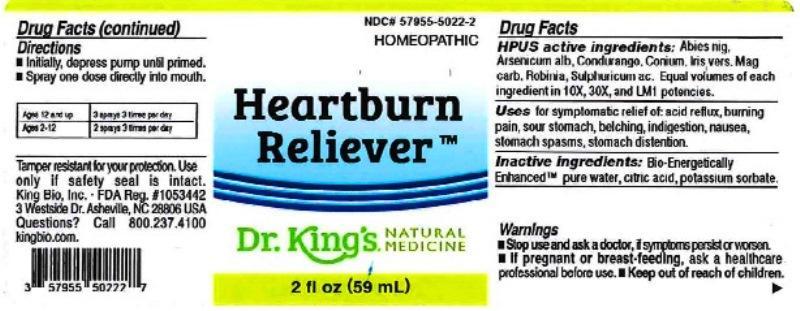 DRUG LABEL: Heartburn Relief
NDC: 57955-5022 | Form: LIQUID
Manufacturer: King Bio Inc.
Category: homeopathic | Type: HUMAN OTC DRUG LABEL
Date: 20161101

ACTIVE INGREDIENTS: PICEA MARIANA RESIN 10 [hp_X]/59 mL; ARSENIC TRIOXIDE 10 [hp_X]/59 mL; MARSDENIA CONDURANGO BARK 10 [hp_X]/59 mL; CONIUM MACULATUM FLOWERING TOP 10 [hp_X]/59 mL; IRIS VERSICOLOR ROOT 10 [hp_X]/59 mL; MAGNESIUM CARBONATE 10 [hp_X]/59 mL; ROBINIA PSEUDOACACIA BARK 10 [hp_X]/59 mL; SULFURIC ACID 10 [hp_X]/59 mL
INACTIVE INGREDIENTS: WATER; ANHYDROUS CITRIC ACID; POTASSIUM SORBATE

Heartburn Relief™

ACTIVE INGREDIENT

Drug Facts__________________________________________________________________________________________________________

HPUS active ingredients: Abies nigra, Arsenicum album, Condurango, Conium maculatum, Iris versicolor, Magnesia carbonica, Robinia pseudoacacia, Sulphuricum acidum. Equal volumes of each ingredient in 10X, 30X, and LM1 potencies.

INDICATIONS AND USAGE

Uses for symptomatic relief of: acid reflux, burning pain, sour stomach, belching, indigestion, nausea, stomach spasms, stomach distention.

Inactive Ingredients:

Bio-Energetically Enhanced™ pure water, citric acid and potassium sorbate.

Warnings

- Stop use and ask your doctor if symptoms persist or worsen.
- If pregnant or breast-feeding, take only on advice of a healthcare professional.

- Keep out of reach of children.

Directions

- Initially, depress pump until primed.
- Spray one dose directly into mouth.
- Ages 12 and up: 3 sprays 3 times per day
- Ages 2-12: 2 sprays 3 times per day

OTHER SAFETY INFORMATION

Tamper resistant for your protection. Use only if safety seal is intact.

PURPOSE

Uses for symptomatic relief of:

- acid reflux
- burning pain
- sour stomach
- belching
- indigestion
- nausea
- stomach spasms
- stomach distention